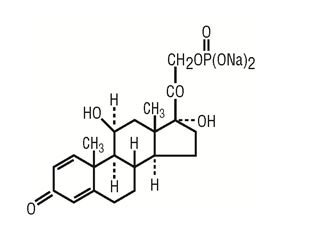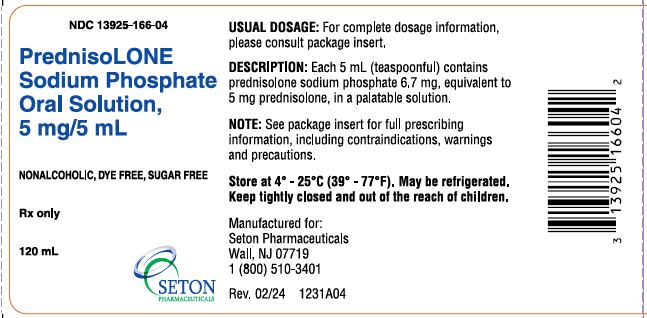 DRUG LABEL: Prednisolone Sodium Phosphate
NDC: 13925-166 | Form: SOLUTION
Manufacturer: Seton Pharmaceuticals, LLC
Category: prescription | Type: HUMAN PRESCRIPTION DRUG LABEL
Date: 20240923

ACTIVE INGREDIENTS: PREDNISOLONE SODIUM PHOSPHATE 5 mg/5 mL
INACTIVE INGREDIENTS: RASPBERRY; SODIUM PHOSPHATE, DIBASIC, HEPTAHYDRATE; SORBITOL; WATER; METHYLPARABEN; EDETATE DISODIUM; SODIUM PHOSPHATE, MONOBASIC

Prednisolone Sodium Phosphate Oral Solution

DESCRIPTION

Prednisolone Sodium Phosphate Oral Solution is a dye free, colorless to light straw-colored, raspberry flavored solution. Each 5 mL (teaspoonful) of Prednisolone Sodium Phosphate Oral Solution contains 6.7 mg prednisolone sodium phosphate (5 mg prednisolone base) in a palatable, aqueous vehicle. Prednisolone Sodium Phosphate Oral Solution also contains dibasic sodium phosphate, edetate disodium, methylparaben, purified water, sodium biphosphate, sorbitol,

natural and artificial raspberry flavor.

Prednisolone sodium phosphate occurs as white or slightly yellow, friable granules or powder. It is freely soluble in water; soluble in methanol; slightly soluble in alcohol and in chloroform; and very slightly soluble in acetone and in dioxane. The chemical name of prednisolone sodium phosphate is: pregna-1,4-diene-3,20-dione,11,17-dihydroxy-21-(phosphonooxy)-,disodium salt,(11()-. The empirical formula is C21H27Na2O8P; the molecular weight is 484.39.

Its chemical structure is:

Pharmacological Category: Glucocorticoid

CLINICAL PHARMACOLOGY

Naturally occurring glucocorticoids (hydrocortisone), which also have salt-retaining properties, are used as replacement therapy in adrenocortical deficiency states. Their synthetic analogs are primarily used for their potent anti-inflammatory effects in disorders of many organ systems.

Prednisolone is a synthetic adrenocortical steroid drug with predominantly glucocorticoid properties. Some of these properties reproduce the physiological actions of endogenous glucocorticosteroids, but others do not necessarily reflect any of the adrenal hormones’ normal functions; they are seen only after administration of large therapeutic doses of the drug. The pharmacological effects of prednisolone which are due to its glucocorticoid properties include: promotion of gluconeogenesis; increased deposition of glycogen in the liver; inhibition of the utilization of glucose; anti-insulin activity; increased catabolism of protein; increased lipolysis; stimulation of fat synthesis and storage; increased glomerular filtration rate and resulting increase in urinary excretion of urate (creatinine excretion remains unchanged); and increased calcium excretion.

Depressed production of eosinophils and lymphocytes occurs, but erythropoiesis and production of polymorphonuclear leukocytes are stimulated. Inflammatory processes (edema, fibrin deposition, capillary dilatation, migration of leukocytes and phagocytosis) and the later stages of wound healing (capillary proliferation, deposition of collagen, cicatrization) are inhibited.

Prednisolone can stimulate secretion of various components of gastric juice. Suppression of the production of corticotropin may lead to suppression of endogenous corticosteroids. Prednisolone has slight mineralocorticoid activity, whereby entry of sodium into cells and loss of intracellular potassium is stimulated. This is particularly evident in the kidney, where rapid ion exchange leads to sodium retention and hypertension.

Prednisolone is rapidly and well absorbed from the gastrointestinal tract following oral administration. Prednisolone Sodium Phosphate Oral Solution produces a 14% higher peak plasma level of prednisolone which occurs 20% faster than that seen with tablets. Prednisolone is 70-90% protein-bound in the plasma and it is eliminated from the plasma with a half-life of 2 to 4 hours. It is metabolized mainly in the liver and excreted in the urine as sulfate and glucuronide conjugates.

The systemic availability, metabolism and elimination of prednisolone after administration of single weight-based doses (0.8 mg/kg) of intravenous (IV) prednisolone and oral prednisone were reported in a small study of 19 young (23 to 34 years) and 12 elderly (65 to 89 years) subjects. Results showed that the systemic availability of total and unbound prednisolone, as well as interconversion between prednisolone and prednisone were independent of age. The mean unbound fraction of prednisolone was higher, and the steady-state volume of distribution (Vss) of unbound prednisolone was reduced in elderly patients. Plasma prednisolone concentrations were higher in elderly subjects, and the higher AUCs of total and unbound prednisolone were most likely reflective of an impaired metabolic clearance, evidenced by reduced fractional urinary clearance of 6(-hydroxyprednisolone. Despite these findings of higher total and unbound prednisolone concentrations, elderly subjects had higher AUCs of cortisol, suggesting that the elderly population is less sensitive to suppression of endogenous cortisol or their capacity for hepatic inactivation of cortisol is diminished.

INDICATIONS AND USAGE

Prednisolone Sodium Phosphate Oral Solution is indicated in the following conditions:

1. Allergic States

Control of severe or incapacitating allergic conditions intractable to adequate trials of conventional treatment in adult and pediatric populations with: seasonal or perennial allergic rhinitis; asthma; contact dermatitis; atopic dermatitis; serum sickness; drug hypersensitivity reactions.

2. Dermatologic Diseases

Pemphigus; bullous dermatitis herpetiformis; severe erythema multiforme (Stevens-Johnson syndrome); exfoliative erythroderma; mycosis fungoides.

3. Edematous States

To induce diuresis or remission of proteinuria in nephrotic syndrome in adults with lupus erythematosus and in adults and pediatric populations, with idiopathic nephrotic syndrome, without uremia.

4. Endocrine Disorders

Primary or secondary adrenocortical insufficiency (hydrocortisone or cortisone is the first choice; synthetic analogs may be used in conjunction with mineralocorticoids where applicable; in infancy mineralocorticoid supplementation is of particular importance); congenital adrenal hyperplasia; hypercalcemia associated with cancer; nonsuppurative thyroiditis.

5. Gastrointestinal Diseases

To tide the patient over a critical period of the disease in: ulcerative colitis; regional enteritis.

6. Hematologic Disorders

Idiopathic thrombocytopenic purpura in adults; selected cases of secondary thrombocytopenia; acquired (autoimmune) hemolytic anemia; pure red cell aplasia; Diamond-Blackfan anemia.

7. Neoplastic Diseases

For the treatment of acute leukemia and aggressive lymphomas in adults and children.

8. Nervous System

Acute exacerbations of multiple sclerosis.

9. Ophthalmic Diseases

Uveitis and ocular inflammatory conditions unresponsive to topical corticosteroids; temporal arteritis; sympathetic ophthalmia.

10. Respiratory Diseases

Symptomatic sarcoidosis; idiopathic eosinophilic pneumonias; fulminating or disseminated pulmonary tuberculosis when used concurrently with appropriate antituberculous chemotherapy; asthma (as distinct from allergic asthma listed above under “Allergic States”), hypersensitivity pneumonitis, idiopathic pulmonary fibrosis, acute exacerbations of chronic obstructive pulmonary disease (COPD), and Pneumocystis carinii pneumonia (PCP) associated with hypoxemia occurring in an HIV (+) individual who is also under treatment with appropriate anti- PCP antibiotics. Studies support the efficacy of systemic corticosteroids for the treatment of these conditions: allergic bronchopulmonary aspergillosis, idiopathic bronchiolitis obliterans with organizing pneumonia.

11. Rheumatic Disorders

As adjunctive therapy for short term administration (to tide the patient over an acute episode or exacerbation) in: psoriatic arthritis; rheumatoid arthritis, including juvenile rheumatoid arthritis (selected cases may require low dose maintenance therapy); ankylosing spondylitis; acute and subacute bursitis; acute nonspecific tenosynovitis; acute gouty arthritis; epicondylitis. For the treatment of systemic lupus erythematosus, dermatomyositis (polymyositis), polymyalgia rheumatica, Sjogren’s syndrome, relapsing polychondritis, and certain cases of vasculitis.

12. Miscellaneous

Tuberculous meningitis with subarachnoid block or impending block, tuberculosis with enlarged mediastinal lymph nodes causing respiratory difficulty, and tuberculosis with pleural or pericardial effusion (appropriate antituberculous chemotherapy must be used concurrently when treating any tuberculosis complications); Trichinosis with neurologic or myocardial involvement; acute or chronic solid organ rejection (with or without other agents).

CONTRAINDICATIONS

Systemic fungal infections.

Hypersensitivity to the drug or any of its components.

WARNINGS

General

In patients on corticosteroid therapy subjected to unusual stress, increased dosage of rapidly acting corticosteroids before, during and after the stressful situation is indicated.

Cardio-renal

Average and large doses of hydrocortisone or cortisone can cause elevation of blood pressure, salt and water retention, and increased excretion of potassium. These effects are less likely to occur with the synthetic derivatives except when used in large doses. Dietary salt restriction and potassium supplementation may be necessary. All corticosteroids increase calcium excretion.

Endocrine

Corticosteroids can produce reversible hypothalamic-pituitary adrenal (HPA) axis suppression with the potential for glucocorticosteroid insufficiency after withdrawal of treatment.

Metabolic clearance of corticosteroids is decreased in hypothyroid patients and increased in hyperthyroid patients. Changes in thyroid status of the patient may necessitate adjustment in dosage.

Infections (General)

Persons who are on drugs which suppress the immune system are more susceptible to infections than healthy individuals. There may be decreased resistance and inability to localize infection when corticosteroids are used. Infection with any pathogen including viral, bacterial, fungal, protozoan or helminthic infection, in any location of the body, may be associated with the use of corticosteroids alone or in combination with other immunosuppressive agents that affect humoral or cellular immunity, or neutrophil function. These infections may be mild to severe, and, with increasing doses of corticosteroids, the rate of occurrence of infectious complications increases. Corticosteroids may also mask some signs of infection after it has already started.

Infections (Viral)

Chicken pox and measles, for example, can have a more serious or even fatal course in non-immune children or adults on corticosteroids. In such children or adults who have not had these diseases, particular care should be taken to avoid exposure. How the dose, route and duration of corticosteroid administration affect the risk of developing a disseminated infection is not known. The contribution of the underlying disease and/or prior corticosteroid treatment to the risk is also not known. If exposed to chicken pox, prophylaxis with varicella zoster immune globulin (VZIG) may be indicated. If exposed to measles, prophylaxis with immunoglobulin (IG) may be indicated. (See the respective package inserts for complete VZIG and IG prescribing information). If chicken pox develops, treatment with antiviral agents should be considered.

Ophthalmic

Use of corticosteroids may produce posterior subcapsular cataracts, glaucoma with possible damage to the optic nerves, and may enhance the establishment of secondary ocular infections due to bacteria, fungi or viruses. The use of oral corticosteroids is not recommended in the treatment of optic neuritis and may lead to an increase in the risk of new episodes. Corticosteroids should not be used in active ocular herpes simplex.

Special Pathogens

Latent disease may be activated or there may be an exacerbation of intercurrent infections due to pathogens, including those caused by Candida, Mycobacterium, Ameba, Toxoplasma, Pneumocystis, Cryptococcus, Nocardia, etc.

Corticosteroids may activate latent amebiasis. Therefore, it is recommended that latent or active amebiasis be ruled out before initiating corticosteroid therapy in any patient who has spent time in the tropics or in any patient with unexplained diarrhea.

Similarly, corticosteroids should be used with great care in patients with known or suspected Strongyloides (threadworm) infestation. In such patients, corticosteroid-induced immunosuppression may lead to Strongyloides hyperinfection and dissemination with widespread larval migration, often accompanied by severe enterocolitis and potentially fatal gram-negative septicemia.

Corticosteroids should not be used in cerebral malaria.

Tuberculosis

The use of prednisolone in active tuberculosis should be restricted to those cases of fulminating or disseminated tuberculosis in which the corticosteroid is used for the management of the disease in conjunction with an appropriate antituberculous regimen.

If corticosteroids are indicated in patients with latent tuberculosis or tuberculin reactivity, close observation is necessary as reactivation of the disease may occur. During prolonged corticosteroid therapy these patients should receive chemoprophylaxis.

Vaccination

Administration of live or live, attenuated vaccines is contraindicated in patients receiving immunosuppressive doses of corticosteroids. Killed or inactivated vaccines may be administered, however, the response to such vaccines can not be predicted. Immunization procedures may be undertaken in patients who are receiving corticosteroids as replacement therapy, e.g., for Addison’s disease.

PRECAUTIONS

General

The lowest possible dose of corticosteroid should be used to control the condition under treatment, and when reduction in dosage is possible, the reduction should be gradual.

Since complications of treatment with glucocorticoids are dependent on the size of the dose and the duration of treatment, a risk/benefit decision must be made in each individual case as to dose and duration of treatment and as to whether daily or intermittent therapy should be used.

There is an enhanced effect of corticosteroids in patients with hypothyroidism and in those with cirrhosis.

Kaposi’s sarcoma has been reported to occur in patients receiving corticosteroid therapy, most often for chronic conditions. Discontinuation of corticosteroids may result in clinical improvement.

Cardio-renal

As sodium retention with resultant edema and potassium loss may occur in patients receiving corticosteroids, these agents should be used with caution in patients with hypertension, congestive heart failure, or renal insufficiency.

Endocrine

Drug-induced secondary adrenocortical insufficiency may be minimized by gradual reduction of dosage. This type of relative insufficiency may persist for months after discontinuation of therapy; therefore, in any situation of stress occurring during that period, hormone therapy should be reinstituted. Since mineralocorticoid secretion may be impaired, salt and/or a mineralocorticoid should be administered concurrently.

Gastrointestinal

Steroids should be used with caution in nonspecific ulcerative colitis, if there is a probability of impending perforation, abscess or other pyogenic infection; diverticulitis; fresh intestinal anastomoses; active or latent peptic ulcer.

Signs of peritoneal irritation following gastrointestinal perforation in patients receiving corticosteroids may be minimal or absent.

Musculoskeletal

Corticosteroids decrease bone formation and increase bone resorption both through their effect on calcium regulation (i.e., decreasing absorption and increasing excretion) and inhibition of osteoblast function. This, together with a decrease in the protein matrix of the bone secondary to an increase in protein catabolism, and reduced sex hormone production, may lead to inhibition of bone growth in children and adolescents and the development of osteoporosis at any age. Special consideration should be given to patients at increased risk of osteoporosis (i.e., postmenopausal women) before initiating corticosteroid therapy.

Neuro-psychiatric

Although controlled clinical trials have shown corticosteroids to be effective in speeding the resolution of acute exacerbations of multiple sclerosis, they do not show that they affect the ultimate outcome or natural history of the disease. The studies do show that relatively high doses of corticosteroids are necessary to demonstrate a significant effect. (See DOSAGE AND ADMINISTRATION)

An acute myopathy has been observed with the use of high doses of corticosteroids, most often occurring in patients with disorders of neuromuscular transmission (e.g., myasthenia gravis), or in patients receiving concomitant therapy with neuromuscular blocking drugs (e.g., pancuronium). This acute myopathy is generalized, may involve ocular and respiratory muscles, and may result in quadriparesis. Elevation of creatinine kinase may occur. Clinical improvement or recovery after stopping corticosteroids may require weeks to years.

Psychic derangements may appear when corticosteroids are used, ranging from euphoria, insomnia, mood swings, personality changes, and severe depression, to frank psychotic manifestations. Also, existing emotional instability or psychotic tendencies may be aggravated by corticosteroids.

Ophthalmic

Intraocular pressure may become elevated in some individuals. If steroid therapy is continued for more than 6 weeks, intraocular pressure should be monitored.

Information for Patients

Patients should be warned not to discontinue the use of Prednisolone Sodium Phosphate Oral Solution abruptly or without medical supervision, to advise any medical attendants that they are taking Prednisolone Sodium Phosphate Oral Solution and to seek medical advice at once should they develop fever or other signs of infection.

Persons who are on immunosuppressant doses of corticosteroids should be warned to avoid exposure to chicken pox or measles. Patients should also be advised that if they are exposed, medical advice should be sought without delay.

Drug Interactions

Drugs such as barbiturates, phenytoin, ephedrine, and rifampin, which induce hepatic microsomal drug metabolizing enzyme activity may enhance metabolism of prednisolone and require that the dosage of Prednisolone Sodium Phosphate Oral Solution be increased.

Increased activity of both cyclosporin and corticosteroids may occur when the two are used concurrently. Convulsions have been reported with this concurrent use.

Estrogens may decrease the hepatic metabolism of certain corticosteroids thereby increasing their effect.

Ketoconazole has been reported to decrease the metabolism of certain corticosteroids by up to 60% leading to an increased risk of corticosteroid side effects.

Coadministration of corticosteroids and warfarin usually results in inhibition of response to warfarin, although there have been some conflicting reports. Therefore, coagulation indices should be monitored frequently to maintain the desired anticoagulant effect.

Concomitant use of aspirin (or other non-steroidal anti-inflammatory agents) and corticosteroids increases the risk of gastrointestinal side effects. Aspirin should be used cautiously in conjunction with corticosteroids in hypoprothrombinemia. The clearance of salicylates may be increased with concurrent use of corticosteroids.

When corticosteroids are administered concomitantly with potassium-depleting agents (i.e., diuretics, amphotericin-B), patients should be observed closely for development of hypokalemia. Patients on digitalis glycosides may be at increased risk of arrhythmias due to hypokalemia.

Concomitant use of anticholinesterase agents and corticosteroids may produce severe weakness in patients with myasthenia gravis. If possible, anticholinesterase agents should be withdrawn at least 24 hours before initiating corticosteroid therapy.

Due to inhibition of antibody response, patients on prolonged corticosteroid therapy may exhibit a diminished response to toxoids and live or inactivated vaccines. Corticosteroids may also potentiate the replication of some organisms contained in live attenuated vaccines. If possible, routine administration of vaccines or toxoids should be deferred until corticosteroid therapy is discontinued.

Because corticosteroids may increase blood glucose concentrations, dosage adjustments of antidiabetic agents may be required.

Corticosteroids may suppress reactions to skin tests.

Pregnancy

Teratogenic Effects

Pregnancy Category C

Prednisolone has been shown to be teratogenic in many species when given in doses equivalent to the human dose. Animal studies in which prednisolone has been given to pregnant mice, rats, and rabbits have yielded an increased incidence of cleft palate in the offspring. There are no adequate and well controlled studies in pregnant women. Prednisolone Sodium Phosphate Oral Solution should be used during pregnancy only if the potential benefit justifies the potential risk to the fetus. Infants born to mothers who have received corticosteroids during pregnancy should be carefully observed for signs of hypoadrenalism.

Nursing Mothers

Systemically administered corticosteroids appear in human milk and could suppress growth, interfere with endogenous corticosteroid production, or cause other untoward effects. Caution should be exercised when Prednisolone Sodium Phosphate Oral Solution is administered to a nursing woman.

Pediatric Use

The efficacy and safety of prednisolone in the pediatric population are based on the well-established course of effect of corticosteroids which is similar in pediatric and adult populations. Published studies provide evidence of efficacy and safety in pediatric patients for the treatment of nephrotic syndrome (>2 years of age), and aggressive lymphomas and leukemias (>1 month of age). However, some of these conclusions and other indications for pediatric use of corticosteroid, e.g., severe asthma and wheezing, are based on adequate and well-controlled trials conducted in adults, on the premises that the course of the diseases and their pathophysiology are considered to be substantially similar in both populations.

The adverse effects of prednisolone in pediatric patients are similar to those in adults (see ADVERSE REACTIONS). Like adults, pediatric patients should be carefully observed with frequent measurements of blood pressure, weight, height, intraocular pressure, and clinical evaluation for the presence of infection, psychosocial disturbances, thromboembolism, peptic ulcers, cataracts, and osteoporosis. Children who are treated with corticosteroids by any route, including systemically administered corticosteroids, may experience a decrease in their growth velocity. This negative impact of corticosteroids on growth has been observed at low systemic doses and in the absence of laboratory evidence of HPA axis suppression (i.e., cosyntropin stimulation and basal cortisol plasma levels). Growth velocity may therefore be a more sensitive indicator of systemic corticosteroid exposure in children than some commonly used tests of HPA axis function. The linear growth of children treated with corticosteroids by any route should be monitored, and the potential growth effects of prolonged treatment should be weighed against clinical benefits obtained and the availability of other treatment alternatives. In order to minimize the potential growth effects of corticosteroids, children should be titrated to the lowest effective dose.

Geriatric Use

Clinical studies of Prednisolone Sodium Phosphate Oral Solution did not include sufficient numbers of subjects aged 65 and over to determine whether they respond differently from younger subjects. Other reported clinical experience with prednisolone sodium phosphate has not identified differences in responses between the elderly and younger patients. However, the incidence of corticosteroid-induced side effects may be increased in geriatric patients and appear to be dose-related. Osteoporosis is the most frequently encountered complication, which occurs at a higher incidence rate in corticosteroid-treated geriatric patients as compared to younger populations and in age-matched controls. Losses of bone mineral density appear to be greatest early on in the course of treatment and may recover over time after steroid withdrawal or use of lower doses (i.e., (5 mg/day). Prednisolone doses of 7.5 mg/day or higher have been associated with an increased relative risk of both vertebral and nonvertebral fractures, even in the presence of higher bone density compared to patients with involutional osteoporosis.

Routine screening of geriatric patients, including regular assessments of bone mineral density and institution of fracture prevention strategies, along with regular review of prednisolone indication should be undertaken to minimize complications and keep the prednisolone dose at the lowest acceptable level. Co-administration of bisphosphonates has been shown to retard the rate of bone loss in corticosteroid-treated males and postmenopausal females, and these agents are recommended in the prevention and treatment of corticosteroid-induced osteoporosis.

It has been reported that equivalent weight-based doses yield higher total and unbound prednisolone plasma concentrations and reduced renal and non-renal clearance in elderly patients compared to younger populations. However, it is not clear whether dosing reductions would be necessary in elderly patients, since these pharmacokinetic alterations may be offset by age-related differences in responsiveness of target organs and/or less pronounced suppression of adrenal release of cortisol. Dose selection for an elderly patient should be cautious, usually staring at the low end of the dosing range, reflecting the greater frequency of decreased hepatic, renal, or cardiac function, and of concomitant disease or other drug therapy.

This drug is known to be substantially excreted by the kidney, and the risk of toxic reactions to this drug may be greater in patients with impaired renal function. Because elderly patients are more likely to have decreased renal function, care should be taken in dose selection, and it may be useful to monitor renal function (see CLINICAL PHARMACOLOGY).

ADVERSE REACTIONS

(listed alphabetically under each subsection):

Cardiovascular:Hypertrophic cardiomyopathy in premature infants.

Dermatologic:Facial erythema; increased sweating; impaired wound healing; may suppress reactions to skin tests; petechiae and ecchymoses; thin fragile skin; urticaria; edema.

Endocrine:Decreased carbohydrate tolerance; development of cushingoid state; hirsutism; increased requirements for insulin or oral hypoglycemic agents in diabetic patients; manifestations of latent diabetes mellitus; menstrual irregularities; secondary adrenocortical and pituitary unresponsiveness, particularly in times of stress, as in trauma, surgery or illness; suppression of growth in children.

Fluid and Electrolyte Disturbances:Congestive heart failure in susceptible patients; fluid retention; hypertension; hypokalemic alkalosis; potassium loss; sodium retention.

Gastrointestinal: Abdominal distention; elevation in serum liver enzyme levels (usually reversible upon discontinuation); pancreatitis; peptic ulcer with possible perforation and hemorrhage; ulcerative esophagitis.

Metabolic: Negative nitrogen balance due to protein catabolism.

Musculoskeletal: Aseptic necrosis of femoral and humeral heads; loss of muscle mass; muscle weakness; osteoporosis; pathologic fracture of long bones; steroid myopathy; tendon rupture; vertebral compression fractures.

Neurological: Convulsions; headache; increased intracranial pressure with papilledema (pseudotumor cerebri) usually following discontinuation of treatment; psychic disorders; vertigo.

Ophthalmic: Exophthalmos; glaucoma; increased intraocular pressure; posterior subcapsular cataracts.

Other: Increased appetite; malaise; nausea; weight gain.

To report SUSPECTED ADVERSE REACTIONS, contact Seton Pharmaceuticals at 1-800-510-3401 or FDA at 1-800-FDA-1088 or www.fda.gov/medwatch.

OVERDOSAGE

The effects of accidental ingestion of large quantities of prednisolone over a very short period of time have not been reported, but prolonged use of the drug can produce mental symptoms, moon face, abnormal fat deposits, fluid retention, excessive appetite, weight gain, hypertrichosis, acne, striae, ecchymosis, increased sweating, pigmentation, dry scaly skin, thinning scalp hair, increased blood pressure, tachycardia, thrombophlebitis, decreased resistance to infection, negative nitrogen balance with delayed bone and wound healing, headache, weakness, menstrual disorders, accentuated menopausal symptoms, neuropathy, fractures, osteoporosis, peptic ulcer, decreased glucose tolerance, hypokalemia, and adrenal insufficiency. Hepatomegaly and abdominal distention have been observed in children.

Treatment of acute overdosage is by immediate gastric lavage or emesis followed by supportive and symptomatic therapy. For chronic overdosage in the face of severe disease requiring continuous steroid therapy the dosage of prednisolone may be reduced only temporarily, or alternate day treatment may be introduced.

DOSAGE AND ADMINISTRATION

The initial dosage of Prednisolone Sodium Phosphate Oral Solution may vary from 5 mL to 60 mL (5 to 60 mg prednisolone base) per day depending on the specific disease entity being treated. In situations of less severity, lower doses will generally suffice while in selected patients higher initial doses may be required. The initial dosage should be maintained or adjusted until a satisfactory response is noted. If after a reasonable period of time, there is a lack of satisfactory clinical response, Prednisolone Sodium Phosphate Oral Solution should be discontinued and the patient placed on other appropriate therapy. IT SHOULD BE EMPHASIZED THAT DOSAGE REQUIREMENTS ARE VARIABLE AND MUST BE INDIVIDUALIZED ON THE BASIS OF THE DISEASE UNDER TREATMENT AND THE RESPONSE OF THE PATIENT. After a favorable response is noted, the proper maintenance dosage should be determined by decreasing the initial drug dosage in small decrements at appropriate time intervals until the lowest dosage which will maintain an adequate clinical response is reached. It should be kept in mind that constant monitoring is needed in regard to drug dosage. Included in the situations which may make dosage adjustments necessary are changes in clinical status secondary to remissions or exacerbations in the disease process, the patient's individual drug responsiveness, and the effect of patient exposure to stressful situations not directly related to the disease entity under treatment; in this latter situation it may be necessary to increase the dosage of Prednisolone Sodium Phosphate Oral Solution for a period of time consistent with the patient’s condition. If after long term therapy the drug is to be stopped, it is recommended that it be withdrawn gradually rather than abruptly.

In the treatment of acute exacerbations of multiple sclerosis, daily doses of 200 mg of prednisolone for a week followed by 80 mg every other day or 4 to 8 mg dexamethasone every other day for one month have been shown to be effective.

In pediatric patients, the initial dose of Prednisolone Sodium Phosphate Oral Solution may vary depending on the specific disease entity being treated. The range of initial doses is 0.14 to 2 mg/kg/day in three or four divided doses (4 to 60 mg/m^2bsa/day).

The standard regimen used to treat nephrotic syndrome in pediatric patients is 60 mg/m2/day given in three divided doses for 4 weeks, followed by 4 weeks of single dose alternate-day therapy at 40 mg/m^2/day.

The National Heart, Lung, and Blood Institute (NHLBI) recommended dosing for systemic prednisone, prednisolone or methylprednisolone in children whose asthma is uncontrolled by inhaled corticosteroids and long-acting bronchodilators is 1-2 mg/kg/day in single or divided doses. It is further recommended that short course, or “burst” therapy, be continued until a child achieves a peak expiratory flow rate of 80% of his or her personal best or symptoms resolve. This usually requires 3 to 10 days of treatment, although it can take longer. There is no evidence that tapering the dose after improvement will prevent a relapse.

For the purpose of comparison, the following is the equivalent milligram dosage of the various glucocorticoids:

Cortisone, 25 | Triamcinolone, 4 | Hydrocortisone, 20 | Paramethasone, 2
Prednisolone, 5 | Betamethasone, 0.75 | Prednisone, 5 | Dexamethasone, 0.75
Methylprednisolone, 4

These dose relationships apply only to oral or intravenous administration of these compounds. When these substances or their derivatives are injected intramuscularly or into joint spaces, their relative properties may be greatly altered.

HOW SUPPLIED

Prednisolone Sodium Phosphate Oral Solution is a colorless to light straw-colored, raspberry flavored solution containing 6.7 mg prednisolone sodium phosphate (5 mg prednisolone base) per 5 mL (teaspoonful).

NDC 13925-166-04

120 mL bottle

Storage and Handling

Store at 4°-25°C (39°-77°F). May be refrigerated. Keep tightly closed and out of the reach of children.

Manufactured for:

Seton Pharmaceuticals

Manasquan, NJ 08736

Rev. 06/13

PACKAGE LABEL.PRINCIPAL DISPLAY PANEL - 5 mg/5mL container label

NDC 13925-166-04

PrednisoLONE
Sodium Phosphate
Oral Solution,
5 mg/5 mL

NONALCOHOLIC, DYE FREE, SUGAR FREE

Rx only

120 mL

SETON PHARMACEUTICALS